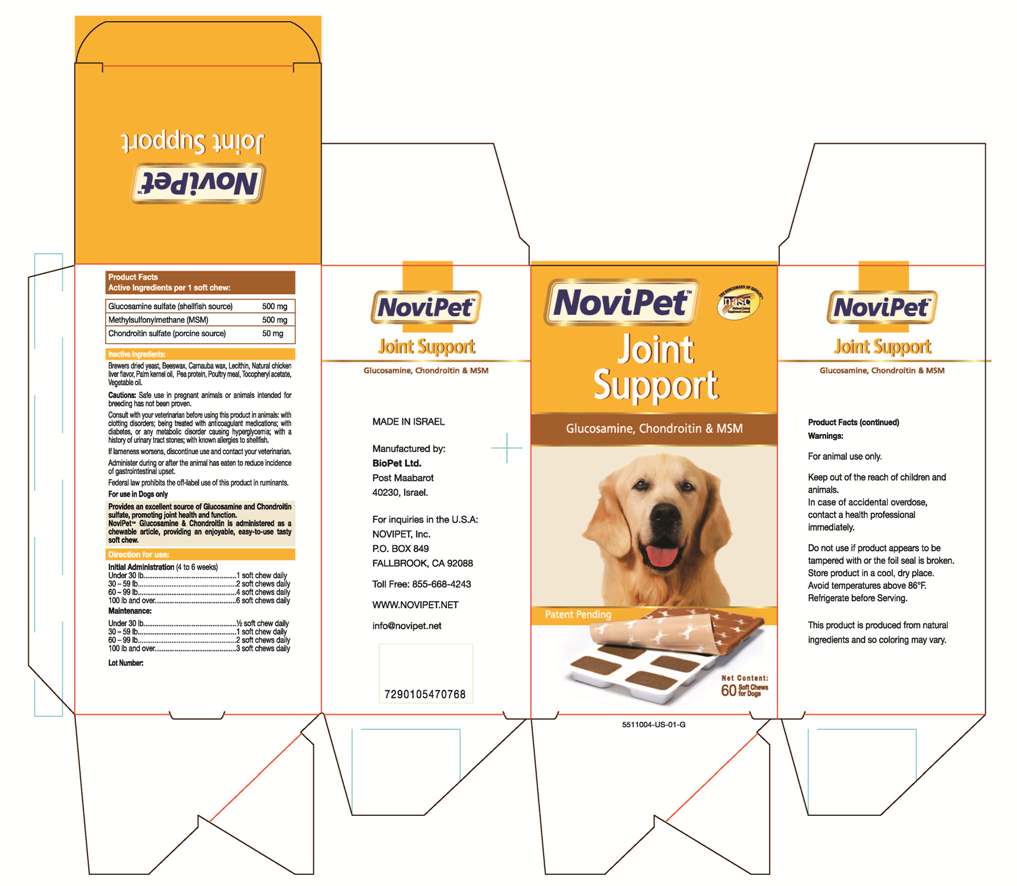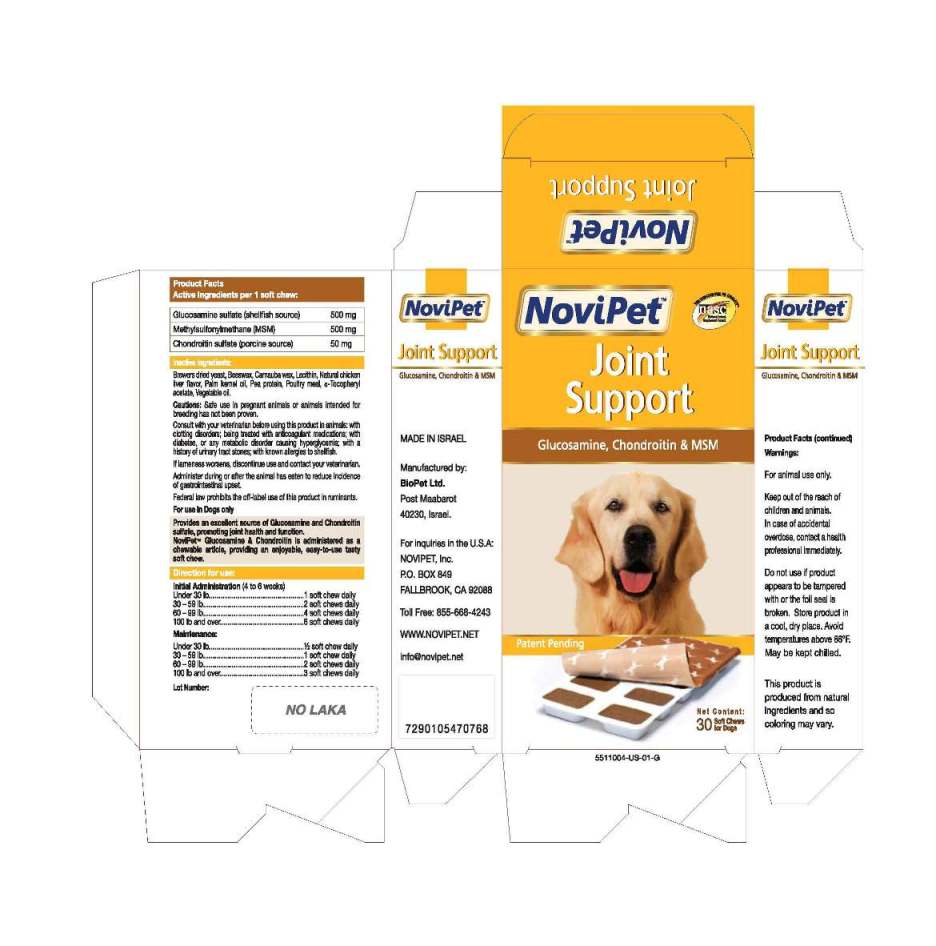 DRUG LABEL: Novipet
NDC: 45732-013 | Form: TABLET, CHEWABLE
Manufacturer: Novipet, Inc.
Category: animal | Type: OTC ANIMAL DRUG LABEL
Date: 20120630

ACTIVE INGREDIENTS: GLUCOSAMINE SULFATE 500 mg/1 1; CHONDROITIN SULFATE SODIUM (PORCINE) 50 mg/1 1; DIMETHYL SULFONE 500 mg/1 1

Novipet Joint Support

FRONT PANEL

NoviPet
Joint
Support
Glucosamine, Chondroitin and MSM
Net Content:
30 Soft Chews for Dogs

Carton left side panel

NoviPet
Joint Support
Glucosamine, Chondrotin and MSM
Made in Israel
Manufactured by:
Biopet Ltd.
Post Maarbarot
40230. Israel
For inquiries in the U.S.A.
Novipet, Inc.
P.O. Box 849
Fallbrook, CA 92088
Toll Free:855-668-4243
www.Novipet.net
Info@novipet.net

Active Ingredients per 1 soft chew
Glucosamine sulfate (shellfish source) 500 mg
Methylsulfonylmethane (MSM) 500 mg
Chondroitin sulfate (porcine source) 50 mg

Inactive Ingredients:
Brewers dried yeast, Beeswax, Carnauba, wax. Lecithin, Natural chicken
liver flavor, Palm Kernel oil, Pea protein, Poultry meal, alpha-Tocopheryl acetate, Vegetable oil.

DOSAGE AND ADMINISTRATION

Directions for use:
Initial Administration (4 to 6 weeks)
Under 30 lb...................1 soft chew daily
30 -59 lb.......................2 soft chews daily
60 -99 lb.......................4 soft chews daily
100 lb and over.. .......... 6 soft chews daily
Maintenance:
Under 30 lb................. 1/2 soft chew daily
30 -59 lb ......................1 soft chew daily
60 -99 lb.......................2 soft Chews daily
100 lb and over.. .......... 3 soft chews daily

Warnings:
For animal use only
Keep out of the reach of
children and animals.
In case of accidental
overdose, contact a health
professional immediately.

WARNINGS AND PRECAUTIONS

Cautions: Safe use in pregnant animals or animals intended for
breeding has not been proven.
Consult with veterinarian before using this product in animals; with
clotting disorders (or being treated with anticoagulant medications); with
diabetes, or any metabolic disorder causing hyperglycemia; with
a history of urinary tract stones; with known allergies to shellfish.
If lameness worsens, discontinue use and contact your veterinarian.
Administer during or after the animal has eaten to reduce incidence
of gastrointestinal upset.
Federal law prohibits the off-label use of this product in ruminants.
For use in Dogs only

Do not use if product appears to be tampered
with or the foil seal is broken.

DESCRIPTION

Provides an excellent source of glucosamine and chondroitin
sulfate, promoting joint health and function.
NoviPet Glucosamine and Chondroitin is administered as a chewable
article, providing an enjoyable, easy-to-use tasty soft chew.

STORAGE AND HANDLING

Store product in a cool, dry place.
Avoid temperatures above 86^0F.
May be kept chilled.
This product is produced from natural
ingredients and so coloring may vary.

PACKAGE LABEL

Novipet Carton

60 NoviPet label